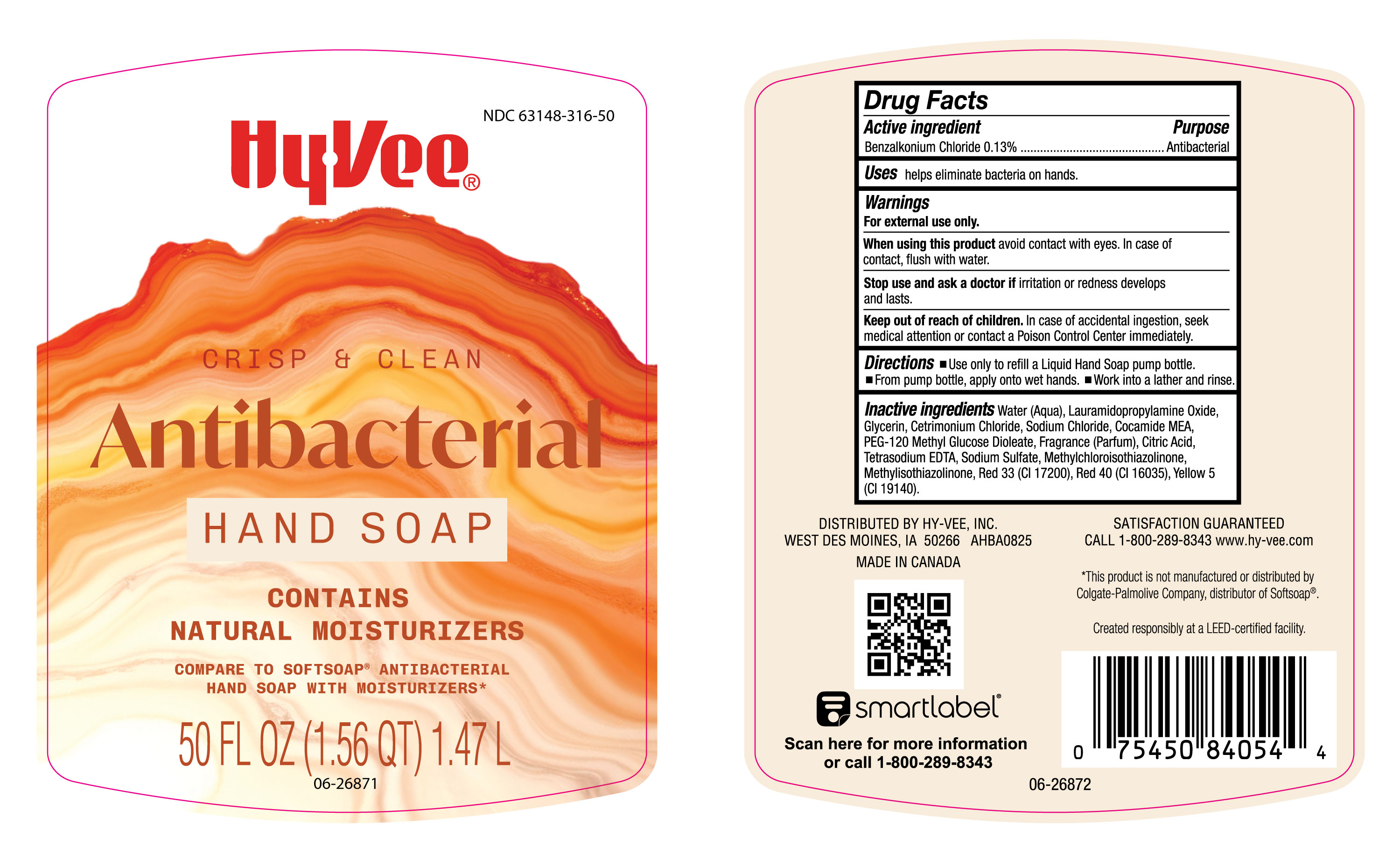 DRUG LABEL: Hy-Vee LHS
NDC: 63148-316 | Form: LIQUID
Manufacturer: Apollo Health and Beauty Care
Category: otc | Type: HUMAN OTC DRUG LABEL
Date: 20260113

ACTIVE INGREDIENTS: BENZALKONIUM CHLORIDE 130 mg/100 mL
INACTIVE INGREDIENTS: CETRIMONIUM CHLORIDE; LAURAMIDOPROPYLAMINE OXIDE; PEG-120 METHYL GLUCOSE DIOLEATE; FD&C RED NO. 40; D&C RED NO. 33; TETRASODIUM EDTA; METHYLCHLOROISOTHIAZOLINONE; SODIUM SULFATE; FRAGRANCE CLEAN ORC0600327; SODIUM CHLORIDE; CITRIC ACID; FD&C YELLOW NO. 5; WATER; GLYCERIN; COCAMIDE MEA; METHYLISOTHIAZOLINONE

NDC- 63148-316, Hy-Vee ANTIBAC LHS.

Active ingredient

Benzalkonium Chloride 0.13%

Purpose

Antibacterial

Uses

helps eliminate bacterial on hands.

Warnings

For external use only

When using this product

avoid contact with eyes. In case of contact, flush with water.

Stop use and ask a doctor if

irritation or redness develops and lasts.

Keep out of reach of children.

In case of accidental ingestion, seek medical attention or contact a Poison Control Center immediately.

Directions

Use only to refill a Liquid Hand Soap pump bottle.

From pump bottle, apply onto wet hands.

Work into a lather and rinse.

Inactive ingredients

Water (Aqua), Lauramidopropylamine Oxide, Glycerin, Cetrimonium Chloride, Sodium Chloride, Cocamide MEA, PEG-120 Methyl Glucose Dioleate, Fragrance (Parfum), Citric Acid, Tetrasodium EDTA, Sodium Sulfate, Methylchloroisothiazolinone, Methylisothiazolinone, Red 33 (CI 17200), Red 40 (CI 16035), Yellow 5 (CI 19140)